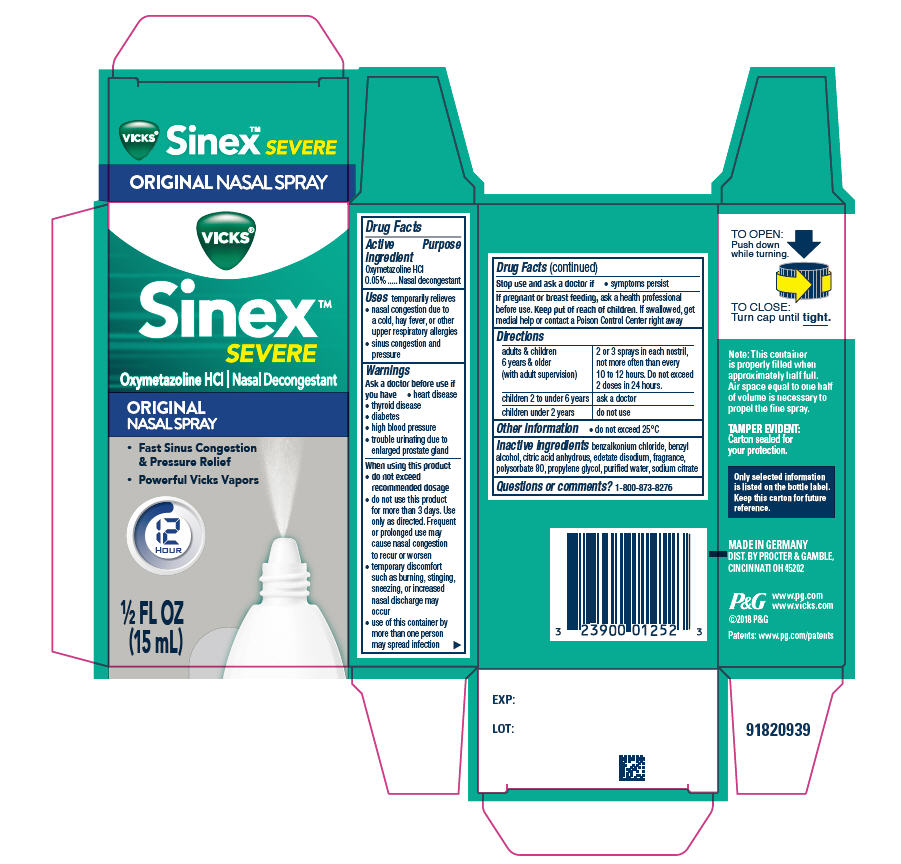 DRUG LABEL: Vicks Sinex Severe
NDC: 64336-170 | Form: SPRAY
Manufacturer: Procter & Gamble Manufacturing GmbH
Category: otc | Type: HUMAN OTC DRUG LABEL
Date: 20251210

ACTIVE INGREDIENTS: OXYMETAZOLINE HYDROCHLORIDE 0.0005095 g/1 mL
INACTIVE INGREDIENTS: PROPYLENE GLYCOL; BENZALKONIUM CHLORIDE; BENZYL ALCOHOL; ANHYDROUS CITRIC ACID; EDETATE DISODIUM; POLYSORBATE 80; WATER; SODIUM CITRATE

Vicks® Sinex™
Severe Original Nasal Spray

Drug Facts

Active ingredient

Oxymetazoline HCl 0.05%

Purpose

Nasal decongestant

Uses

temporarily relieves

- nasal congestion due to a cold, hay fever, or other upper respiratory allergies
- sinus congestion and pressure

Warnings

Ask a doctor before use if you have

- heart disease
- thyroid disease
- diabetes
- high blood pressure
- trouble urinating due to enlarged prostate gland

When using this product

- do not exceed recommended dosage
- do not use this product for more than 3 days. Use only as directed. Frequent or prolonged use may cause nasal congestion to recur or worsen
- temporary discomfort such as burning, stinging, sneezing, or increased nasal discharge may occur
- use of this container by more than one person may spread infection

Stop use and ask a doctor if

- symptoms persist.

PREGNANCY OR BREAST FEEDING

If pregnant or breast-feeding, ask a health professional before use.

Keep out of reach of children.

If swallowed, get medical help or contact a Poison Control Center right away

Directions

adults & children 6 years & older (with adult supervision) | 2 or 3 sprays in each nostril, not more often than every 10 to 12 hours. Do not exceed 2 doses in 24 hours.
children 2 to under 6 years | ask a doctor
children under 2 years | do not use

Other information

- do not exceed 25ºC

Inactive ingredients

benzalkonium chloride, benzyl alcohol, citric acid anhydrous, edetate disodium, fragrance, polysorbate 80, propylene glycol, purified water, sodium citrate

Questions?

1-800-873-8276

TAMPER EVIDENT: Carton sealed for your protection.

MADE IN GERMANY
DIST. BY PROCTER & GAMBLE,
CINCINNATI OH 45202

PRINCIPAL DISPLAY PANEL - 15 ml Bottle Carton

VICKS®

Sinex™

SEVERE

Oxymetazoline HCl Nasal Decongestant

ORIGNAL

NASAL SPRAY

- Fast Sinus Congestion & Pressure Relief
- Powerful Vicks Vapors

12
HOUR

½ FL OZ
(15 ml)